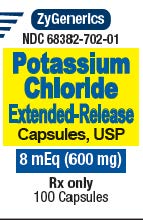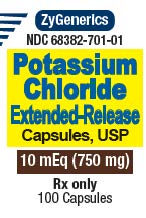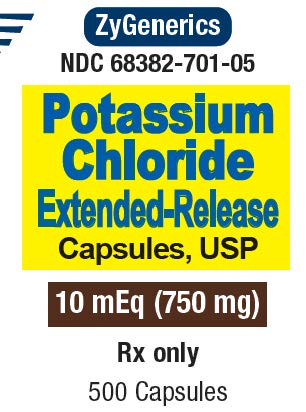 DRUG LABEL: POTASSIUM CHLORIDE
NDC: 68382-702 | Form: CAPSULE, EXTENDED RELEASE
Manufacturer: Zydus Pharmaceuticals (USA) Inc. 
Category: prescription | Type: HUMAN PRESCRIPTION DRUG LABEL
Date: 20211217

ACTIVE INGREDIENTS: POTASSIUM CHLORIDE 600 mg/1 1
INACTIVE INGREDIENTS: ETHYLCELLULOSES; FD&C BLUE NO. 2; FD&C YELLOW NO. 6; GELATIN; MAGNESIUM STEARATE; SODIUM LAURYL SULFATE; TITANIUM DIOXIDE; FD&C RED NO. 40; ALUMINUM OXIDE

HIGHLIGHTS OF PRESCRIBING INFORMATION

These highlights do not include all the information needed to use POTASSIUM CHLORIDE EXTENDED-RELEASE CAPSULES safely and effectively. See full prescribing information for POTASSIUM CHLORIDE EXTENDED-RELEASE CAPSULES
Initial U.S. Approval: 1948

1 INDICATIONS AND USAGE

Potassium Chloride Extended-Release Capsules, USP contain potassium chloride, a potassium salt indicated for the treatment and prophylaxis of hypokalemia with or without metabolic alkalosis, in patients for whom dietary management with potassium-rich foods or diuretic does reduction is insufficient. (1)

2 DOSAGE AND ADMINISTRATION

Monitor serum potassium and adjust dosage accordingly (2.1)

If serum potassium concentration is <2.5 mEq/L, use intravenous potassium instead of oral supplementation (2.1)

Treatment of hypokalemia:

- Adults: Typical doses range from 40-100 mEq/day in 2-5 divided doses; limit doses to 40 mEq per dose. (2.2)
- Pediatric patients: 2-4 mEq/kg/day in divided doses not to exceed 1 mEq/kg as a single dose or 20 mEq, whichever is lower; if deficits are severe or ongoing losses are great, consider intravenous therapy. (2.3)

Maintenance or Prophylaxis of hypokalemia:

- Adults: Typical dose is 20 mEq per day (2.2)
- Pediatric patients: Typical dose is 1 mEq/kg/day. (2.3)

3 DOSAGE FORMS AND STRENGTHS

- Extended-release capsules: 600 mg (8 mEq) and 750 mg (10 mEq)

4 CONTRAINDICATIONS

- Concomitant use with triamterene and amiloride. (4)

5 WARNINGS AND PRECAUTIONS

- Gastrointestinal Irritation: Take with meals (5.1)

6 ADVERSE REACTIONS

Most common adverse reactions are nausea, vomiting, flatulence, abdominal pain/discomfort, and diarrhea. (6)

To report SUSPECTED ADVERSE REACTIONS, contact Zydus Pharmaceuticals USA Inc. at 1-877-993-8779 or FDA at 1-800-FDA-1088 or www.fda.gov/medwatch.

7 DRUG INTERACTIONS

- Triamterene and amiloride: Concomitant use is contraindicated (7.1)
- Renin-angiotensin-aldosterone inhibitors: Monitor for hyperkalemia (7.2)
- Nonsteroidal Anti-inflammatory drugs (NSAIDS): Monitor for hyperkalemia (7.3)

8 USE IN SPECIFIC POPULATIONS

- Cirrhosis: Initiate therapy at the low end of the dosing range (8.6)
- Renal Impairment: Initiate therapy at the low end of the dosing range (8.7)

FULL PRESCRIBING INFORMATION

1 INDICATIONS AND USAGE

Potassium chloride extended-release capsules are indicated for the treatment and prophylaxis of hypokalemia in adults and children with or without metabolic alkalosis, in patients for whom dietary management with potassium-rich foods or diuretic dose reduction is insufficient.

2 DOSAGE AND ADMINISTRATION

2.1 Administration and Monitoring

If serum potassium concentration is <2.5 mEq/L, use intravenous potassium instead of oral supplementation.

Monitoring

Monitor serum potassium and adjust dosages accordingly. Monitor serum potassium periodically during maintenance therapy to ensure potassium remains in desired range.

The treatment of potassium depletion, particularly in the presence of cardiac disease, renal disease, or acidosis requires careful attention to acid-base balance, volume status, electrolytes, including magnesium, sodium, chloride, phosphate, and calcium, electrocardiograms and the clinical status of the patient. Correct volume status, acid-base balance and electrolyte deficits as appropriate.

Administration

Take with meals and with a full glass of water or other liquid. Do not take on an empty stomach because of the potential for gastric irritation. (5.1)

Patients who have difficulty swallowing capsules may sprinkle the contents of the capsule onto a spoonful of soft food. The soft food, such as applesauce or pudding, should be swallowed immediately without chewing and followed with a glass of water or juice to ensure complete swallowing of the microcapsules. Do not added to hot foods. Any microcapsule/food mixture should be used immediately and not stored for future use.

2.2 Adult Dosing

Dosage must be adjusted to the individual needs of each patient. Dosages greater than 40 mEq per day should be divided such that no more than 40 mEq is given in a single dose.

Treatment of hypokalemia: Typical dose range is 40-100 mEq per day.

Maintenance or Prophylaxis: Typical dose is 20 mEq per day.

2.3 Pediatric Dosing

Pediatric patients aged birth to 16 years old: Dosage must be adjusted to the individual needs of each patient. Do not exceed as a single dose 1 mEq/kg or 20 mEq, whichever is lower.

Treatment of hypokalemia: The recommended initial dose is 2 to 4 mEq/kg/day in divided doses. If deficits are severe or ongoing losses are great, consider intravenous therapy.

Maintenance or Prophylaxis: Typical dose is 1 mEq/kg/day.

3 DOSAGE FORMS AND STRENGTHS

600 mg (8 mEq): Opaque pale orange capsules imprinted in black ink "002" on the cap and "002" on the body.

750 mg (10 mEq): Opaque pale orange/opaque white capsules imprinted in black ink "001" on the cap and "001" on the body.

4 CONTRAINDICATIONS

Potassium chloride extended-release capsules are contraindicated in patients on amiloride or triamterene.

5 WARNINGS AND PRECAUTIONS

Because of reports of intestinal and gastric ulceration and bleeding with controlled-release potassium chloride preparations, these drugs should be reserved for those patients who cannot tolerate or refuse to take liquid or effervescent potassium preparations or for patients in whom there is a problem of compliance with these preparations.

1. For the treatment of patients with hypokalemia, with or without metabolic alkalosis, in digitalis intoxications, and in patients with hypokalemic familial periodic paralysis. If hypokalemia is the result of diuretic therapy, consideration should be given to the use of a lower dose of diuretic, which may be sufficient without leading to hypokalemia.
2. For the prevention of hypokalemia in patients who would be at particular risk if hypokalemia were to develop (e.g., digitalized patients or patients with significant cardiac arrhythmias, hepatic cirrhosis with ascites, states of aldosterone excess with normal renal function, potassium-losing nephropathy, and certain diarrheal states).

The use of potassium salts in patients receiving diuretics for uncomplicated essential hypertension is often unnecessary when such patients have a normal dietary pattern and when low doses of the diuretic are used. Serum potassium should be checked periodically, however, and if hypokalemia occurs, dietary supplementation with potassium-containing foods may be adequate to control milder cases. In more severe cases, and if dose adjustment of the diuretic is ineffective or unwarranted, supplementation with potassium salts may be indicated.

Hyperkalemia [see Overdosage (10)].

In patients with impaired mechanisms for excreting potassium, the administration of potassium salts can produce hyperkalemia and cardiac arrest. This occurs most commonly in patients given potassium by the intravenous route, but may also occur in patients given potassium orally. Potentially fatal hyperkalemia can develop rapidly and be asymptomatic. The use of potassium salts in patients with chronic renal disease, or any other condition which impairs potassium excretion, requires particularly careful monitoring of the serum potassium concentration and appropriate dosage adjustments.

5.1 Gastrointestinal Adverse Reactions

Solid oral dosage forms of potassium chloride can produce ulcerative and/or stenotic lesions of the gastrointestinal tract, particularly if the drug is in contact with the gastrointestinal mucosa for a prolonged period of time. Consider the use of liquid potassium in patients with dysphagia, swallowing disorders, or severe gastrointestinal motility disorders.

If severe vomiting, abdominal pain, distention, or gastrointestinal bleeding occurs, discontinue potassium chloride extended-release capsules and consider possibility of ulceration, obstruction or perforation.

Potassium chloride extended-release capsules should not be taken on an empty stomach because of its potential for gastric irritation [see Dosage and Administration (2.1)].

6 ADVERSE REACTIONS

The following adverse reactions have been identified with use of oral potassium salts. Because these reactions are reported voluntarily from a population of uncertain size, it is not always possible to reliably estimate their frequency or establish a causal relationship to drug exposure.

The most common adverse reactions to oral potassium salts are nausea, vomiting, flatulence, abdominal pain/discomfort, and diarrhea.

There have been reports of hyperkalemia and of upper and lower gastrointestinal conditions including, obstruction, bleeding, ulceration, and perforation.

Skin rash has been reported rarely.

7 DRUG INTERACTIONS

7.1 Amiloride and Triamterene

Use with triamterene or amiloride can produce severe hyperkalemia. Concomitant use is contraindicated [see Contraindications (4)].

7.2 Renin-angiotensin-aldosterone inhibitors

Drugs that inhibit the renin-angiotensin-aldosternone system (RAAS) including angiotensin converting enzyme (ACE) inhibitors, angiotensin receptor blockers (ARBs), spironolactone, eplerenone, or aliskiren produces potassium retention by inhibiting aldosterone production. Closely monitor potassium in patients taking drugs that inhibit RAAS.

7.3 Nonsteroidal Anti-Inflammatory Drugs (NSAIDs)

NSAIDs may produce potassium retention by reducing renal synthesis of prostaglandin E and impairing the renin-angiotensin system. Closely monitor potassium in patients taking NSAIDS.

8 USE IN SPECIFIC POPULATIONS

8.1 Pregnancy

Risk Summary

There are no human data related to use of potassium chloride extended-release capsules during pregnancy and animal reproductive studies have not been conducted. Potassium supplementation that does not lead to hyperkalemia is not expected to cause fetal harm.

The background risk for major birth defects and miscarriage in the indicated population is unknown. All pregnancies have a background risk of birth defect, loss, or other adverse outcomes. In the U.S. general population, the estimated background risk of major birth defects and miscarriage in clinically recognized pregnancies is 2-4% and 15-20%, respectively.

8.2 Lactation

Risk Summary

The normal potassium ion content of human milk is about 13 mEq per liter. Since oral potassium becomes part of the body potassium pool, as long as body potassium is not excessive, the contribution of potassium chloride supplementation should have little or no effect on the level in human milk.

8.4 Pediatric Use

Clinical trial data from published literature have demonstrated the safety and effectiveness of potassium chloride in children with diarrhea and malnutrition from birth to 18 years.

8.5 Geriatric Use

Clinical studies of potassium chloride did not include sufficient numbers of subjects aged 65 and over to determine whether they respond differently from younger subjects. Other reported clinical experience has not identified differences in responses between the elderly and younger patients. In general, dose selection for an elderly patient should be cautious, usually starting at the low end of the dosing range, reflecting the greater frequency of decreased hepatic, renal, or cardiac function, and of concomitant disease or other drug therapy.

This drug is known to be substantially excreted by the kidney, and the risk of toxic reactions to this drug may be greater in patients with impaired renal function. Because elderly patients are more likely to have decreased renal function, care should be taken in dose selection, and it may be useful to monitor renal function.

8.6 Cirrhotics

Based on publish literature, the baseline corrected serum concentrations of potassium measured over 3 hours after administration in cirrhotic subjects who received an oral potassium load rose to approximately twice that of normal subjects who received the same load. Patients with cirrhosis should usually be started at the low end of the dosing range, and the serum potassium level should be monitored frequently [see Clinical Pharmacology (12.3)].

8.7 Renal Impairment

Patients with renal impairment have reduced urinary excretion of potassium and are at substantially increased risk of hyperkalemia. Patients with impaired renal function, particularly if the patient is on RAAS inhibitors or nonsteroidal anti-inflammatory drugs, should usually be started at the low end of the dosing range because of the potential for development of hyperkalemia [see Drug Interactions (7.2), (7.3)]. The serum potassium level should be monitored frequently. Renal function should be assessed periodically.

10 OVERDOSAGE

10.1 Symptoms

The administration of oral potassium salts to persons with normal excretory mechanisms for potassium rarely causes serious hyperkalemia. However, if excretory mechanisms are impaired, potentially fatal hyperkalemia can result.

Hyperkalemia is usually asymptomatic and may be manifested only by an increased serum potassium concentration (6.5-8.0 mEq/L) and characteristic electrocardiographic changes (peaking of T-waves, loss of P-waves, depression of S-T segment, and prolongation of the QT-interval). Late manifestations include muscle paralysis and cardiovascular collapse from cardiac arrest (9-12 mEq/L).

10.2 Treatment

Treatment measures for hyperkalemia include the following:

1. Monitor closely for arrhythmias and electrolyte changes.
2. Eliminate foods and medications containing potassium and any agents with potassium-sparing properties such as potassium-sparing diuretics, ARBs, ACE inhibitors, NSAIDs, certain nutritional supplements, and many others.
3. Administer intravenous calcium gluconate if the patient is at no risk or low risk of developing digitalis toxicity.
4. Administer 300 to 500 mL/hr of 10% dextrose solution containing 10 to 20 units of crystalline insulin per 1,000 mL.
5. Correct acidosis, if present, with intravenous sodium bicarbonate.
6. Use exchange resins, hemodialysis, or peritoneal dialysis.

In patients who have been stabilized on digitalis, too rapid a lowering of the serum potassium concentration can produce digitalis toxicity.

The extended-release feature means that absorption and toxic effects may be delayed for hours. Consider standard measures to remove any unabsorbed drug.

11 DESCRIPTION

Potassium chloride extended-release capsules are an oral dosage form of microencapsulated potassium chloride containing 600 mg and 750 mg of potassium chloride, USP, equivalent to 8 mEq and 10 mEq of potassium, respectively.

The chemical name of the active ingredient is potassium chloride and the structural formula is KCl. It has a molecular mass of 74.55. Potassium chloride, USP, occurs as a white granular powder or as colorless crystals. It is odorless and has a saline taste. Its solutions are neutral to litmus. It is freely soluble in water and insoluble in alcohol.

Inactive ingredients: edible ink, ethylcellulose, FD&C Blue No. 2 aluminum lake, FD&C Yellow No. 6, gelatin, magnesium stearate, sodium lauryl sulfate, titanium dioxide. May contain FD&C Red No. 40 and FD&C Yellow No. 6 aluminum lakes.

12 CLINICAL PHARMACOLOGY

12.1 Mechanism of Action

The potassium ion (K^+) is the principal intracellular cation of most body tissues. Potassium ions participate in a number of essential physiological processes, including the maintenance of intracellular tonicity; the transmission of nerve impulses; the contraction of cardiac, skeletal, and smooth muscle; and the maintenance of normal renal function.

The intracellular concentration of potassium is approximately 150 to 160 mEq per liter. The normal adult plasma concentration is 3.5 to 5 mEq per liter. An active ion transport system maintains this gradient across the plasma membrane.

Potassium is a normal dietary constituent and under steady-state conditions the amount of potassium absorbed from the gastrointestinal tract is equal to the amount excreted in the urine. The usual dietary intake of potassium is 50 to 100 mEq per day.

12.3 Pharmacokinetics

Each crystal of KCl is microencapsulated and allows for the controlled release of potassium and chloride ions over an eight- to ten-hour period.

Specific Populations

Cirrhotics

Based on publish literature, the baseline corrected serum concentrations of potassium measured over 3 hours after administration in cirrhotic subjects who received an oral potassium load rose to approximately twice that of normal subjects who received the same load.

16 HOW SUPPLIED/STORAGE AND HANDLING

Potassium chloride extended-release capsules contain 600 mg and 750 mg of potassium chloride (equivalent to 8 mEq and 10 mEq, respectively):

Table 1: How Supplied
Dose | Color | Printing | NDC#:68382-xxx-xx
Dose | Color | Printing | Bottle Count
Dose | Color | Printing | 100 | 500
600 mg (8 mEq) | Orange | "002" - body | 702-01 | 702-05
600 mg (8 mEq) | Orange | "002" - cap | 702-01 | 702-05
750 mg (10 mEq) | White | "001" – body | 701-01 | 701-05
750 mg (10 mEq) | White | "001" - cap | 701-01 | 701-05

17 PATIENT COUNSELING INFORMATION

- Inform patients to take each dose with meals and with a full glass of water or other liquid.
- Advise patients seek medical attention if tarry stools or other evidence of gastrointestinal toxicity is noticed.

Store at 20°-25°C (68°-77°F); excursions are permitted to 15° to 20°C (59°-86°F) [see USP Controlled Room Temperature.]

Dispense in tight, light-resistant container as defined in the USP, with a child-resistant closure.

Rx only

Manufactured and Distributed By:

Nesher Pharmaceuticals USA LLC.

St. Louis, MO 63044

Distributed By:

Zydus Pharmaceuticals USA Inc.

Pennington, NJ 08534

Part #: RA-SUB2

Revised 04/2018

PACKAGE LABEL.PRINCIPAL DISPLAY PANEL

ZyGenerics

NDC 68382-702-01

Potassium Chloride Extended-Release Capsules, USP

8 mEq (600 mg)

Rx only

100 Capsules

ZyGenerics

NDC 68382-701-01

Potassium Chloride Extended-Release Capsules, USP

10 mEq (750 mg)

Rx only

100 Capsules

ZyGenerics

NDC 68382-701-05

Potassium Chloride Extended-Release Capsules, USP

10 mEq (750 mg)

Rx only

500 Capsules